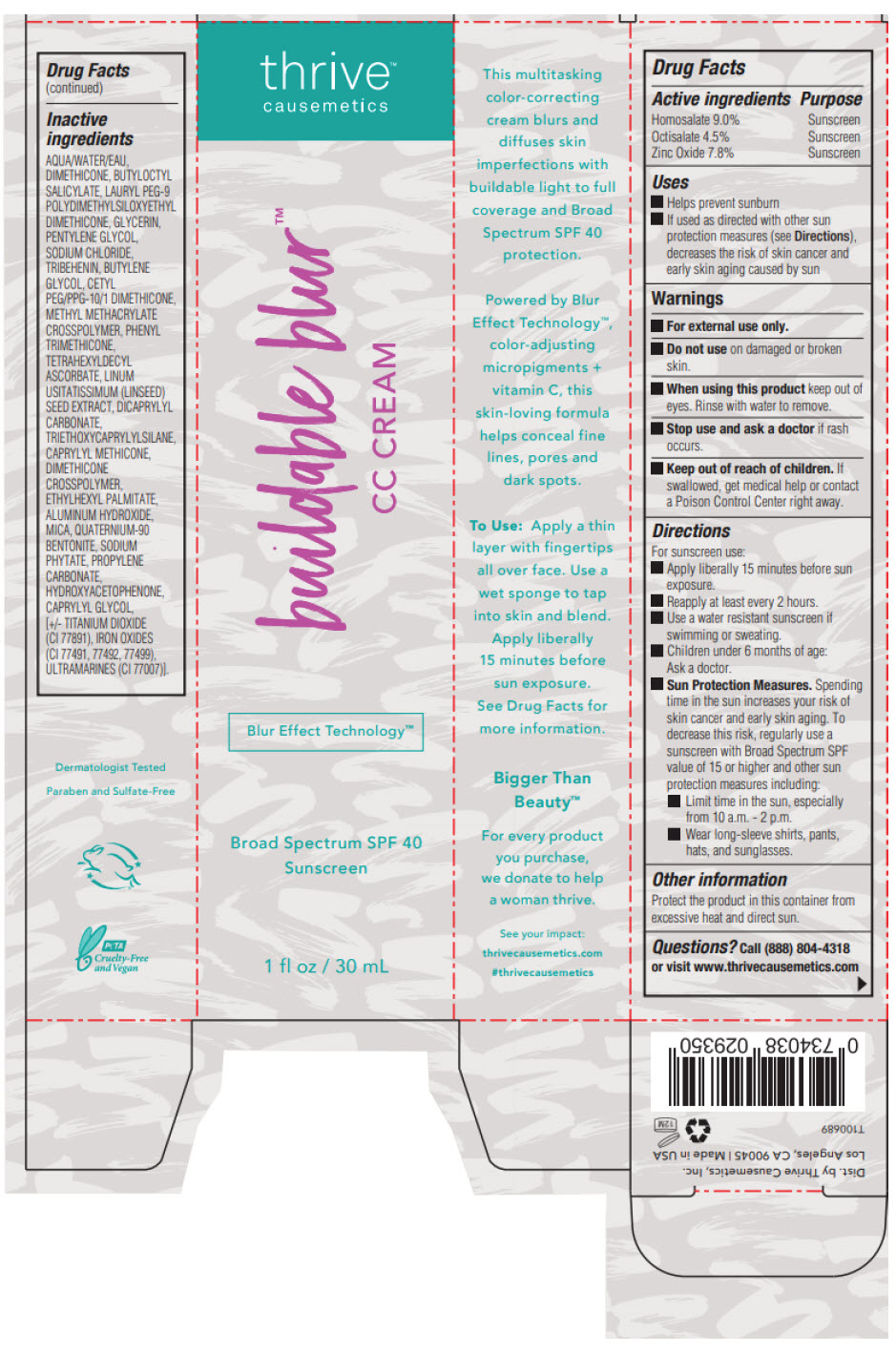 DRUG LABEL: Buildable Blur CC Broad Spectrum SPF 40 Sunscreen
NDC: 77365-005 | Form: CREAM
Manufacturer: Thrive Causemetics
Category: otc | Type: HUMAN OTC DRUG LABEL
Date: 20241105

ACTIVE INGREDIENTS: Homosalate 90 mg/1 mL; Octisalate 45 mg/1 mL; Zinc Oxide 78 mg/1 mL
INACTIVE INGREDIENTS: WATER; DIMETHICONE; BUTYLOCTYL SALICYLATE; LAURYL PEG-9 POLYDIMETHYLSILOXYETHYL DIMETHICONE; GLYCERIN; PENTYLENE GLYCOL; SODIUM CHLORIDE; TRIBEHENIN; BUTYLENE GLYCOL; CETYL PEG/PPG-10/1 DIMETHICONE (HLB 4); METHYL METHACRYLATE/GLYCOL DIMETHACRYLATE CROSSPOLYMER; PHENYL TRIMETHICONE; TETRAHEXYLDECYL ASCORBATE; FLAX SEED; DICAPRYLYL CARBONATE; TRIETHOXYCAPRYLYLSILANE; CAPRYLYL TRISILOXANE; DIMETHICONE CROSSPOLYMER (450000 MPA.S AT 12% IN CYCLOPENTASILOXANE); ETHYLHEXYL PALMITATE; ALUMINUM HYDROXIDE; MICA; QUATERNIUM-90 BENTONITE; PHYTATE SODIUM; PROPYLENE CARBONATE; HYDROXYACETOPHENONE; CAPRYLYL GLYCOL; TITANIUM DIOXIDE; FERRIC OXIDE RED; FERRIC OXIDE YELLOW; FERROSOFERRIC OXIDE; ULTRAMARINE BLUE

Buildable Blur™ CC Cream Broad Spectrum SPF 40 Sunscreen

Drug Facts

ACTIVE INGREDIENT

Active ingredients | Purpose
Homosalate 9.0% | Sunscreen
Octisalate 4.5% | Sunscreen
Zinc Oxide 7.8% | Sunscreen

Uses

- Helps prevent sunburn
- If used as directed with other sun protection measures (see Directions), decreases the risk Skin cancer and early skin aging caused by the sun.

Warnings

- For external use only.

- Do not use on damaged or broken skin.

- When using this product keep out of eyes. Rinse with water to remove

- Stop use and ask a doctor if rash occurs.

- Keep out of reach of children. If swallowed, get medical help or contact a Poison Control Center right away.

Directions

For sunscreen use:

- Apply liberally 15 minutes before sun exposure.
- Reapply at least every 2 hours.
- Use a water resistant sunscreen if swimming or sweating.
- Sun Protection Measures: Spending time in the sun increases your risk of skin cancer and early skin aging. To decrease this risk regularly use a sunscreen with a Broad Spectrum SPF value of 15 or higher and other sun protection measures including:
  - Limit time in the sun, especially from 10 am. - 2 pm.
  - Wear long-sleeved shirts, pants, and sunglasses.
- Children under 6 months of age: Ask a doctor.

Other information

- Protect this product in this container from excessive heat and direct sun.

Inactive ingredients

AQUA/WATER/EAU, DIMETHICONE, BUTYLOCTYL SALICYLATE, LAURYL PEG-9 POLYDIMETHYLSILOXYETHYL DIMETHICONE, GLYCERIN, PENTYLENE GLYCOL, SODIUM CHLORIDE, TRIBEHENIN, BUTYLENE GLYCOL, CETYL PEG/PPG-10/1 DIMETHICONE, METHYL METHACRYLATE CROSSPOLYMER, PHENYL TRIMETHICONE, TETRAHEXYLDECYL ASCORBATE, LINUM USITATISSIMUM (LINSEED) SEED EXTRACT, DICAPRYLYL CARBONATE, TRIETHOXYCAPRYLYLSILANE, CAPRYLYL METHICONE, DIMETHICONE CROSSPOLYMER, ETHYLHEXYL PALMITATE, ALUMINUM HYDROXIDE, MICA, QUATERNIUM-90 BENTONITE, SODIUM PHYTATE, PROPYLENE CARBONATE, HYDROXYACETOPHENONE, CAPRYLYL GLYCOL, [+/- TITANIUM DIOXIDE (CI 77891), IRON OXIDES (CI 77491, 77492, 77499), ULTRAMARINES (CI 77007)].

Questions?

Call (888) 804-4318 or visit www.thrivecausemetics.com

Dist. by Thrive Causemetics, Inc.
Los Angeles, CA 90045

PRINCIPAL DISPLAY PANEL - 30 mL Tube Box

thrive™
causemetics

buildable blur™
CC CREAM

Blur Effect Technology™

Broad Spectrum SPF 40
Sunscreen

1 fl oz / 30 mL